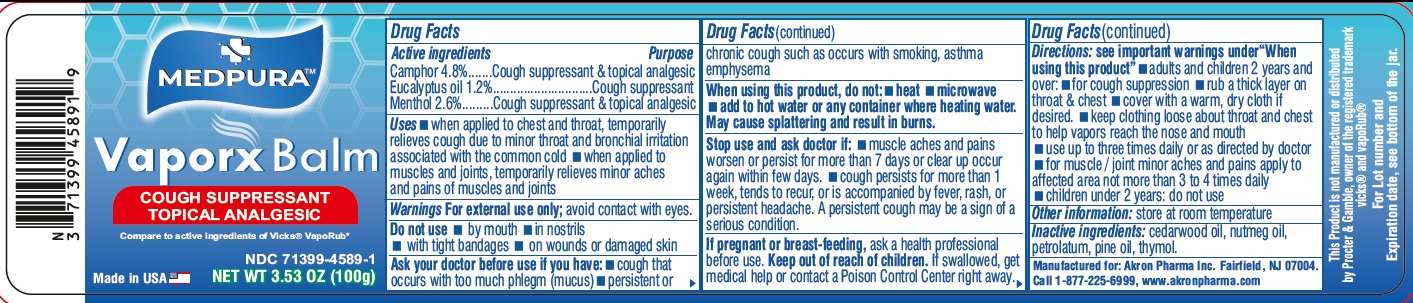 DRUG LABEL: VAPORX
NDC: 71399-4589 | Form: OINTMENT
Manufacturer: AKRON PHARMA INC
Category: otc | Type: HUMAN OTC DRUG LABEL
Date: 20260119

ACTIVE INGREDIENTS: CAMPHOR (SYNTHETIC) 0.048 g/1 g; EUCALYPTUS OIL 0.012 g/1 g; MENTHOL 0.026 g/1 g
INACTIVE INGREDIENTS: CEDAR LEAF OIL; NUTMEG OIL; PETROLATUM; PINE NUT OIL; THYMOL

MEDPURA
VaporX Balm

Drug Facts

Active ingredients

Camphor 4.8%
Eucalyptus oil 1.2%
Menthol 2.6%

Purpose

Cough suppressant and topical analgesic

Cough suppressant

Cough suppressant and topical analgesic

Uses

- when applied to chest and throat, temporarily relieves cough due to minor throat and bronchial irritation associatedwith the common cold
- when applied to muscles and joints, temporarily relieves minor aches and pains of muscles and joints

Warnings

For external use only;avoid contact with eyes.

Do not use

- by mouth
- in nostrils
- with tight bandages
- on wounds or damaged skin

Ask a doctor before use if you have

- cough that occurs with too much phlegm (mucus)
- persistent or chronic cough such as occurs with smoking, asthma or emphysema

When using this product, do not

- heat
- microwave
- add to hot water or any container where heating water. May cause splattering and result in burns.

Stop use and ask a doctor if

- muscle aches and pains worsen or persist for more than 7 days or clear up occur again within few days.
- cough persists for more than 1 week, tends to recur, or is accompanied by fever, rash, or persistent headache. A persistent cough may be a sign of a serious condition.

PREGNANCY OR BREAST FEEDING

If pregnant or breast-feeding,ask a health professional before use.

Keep out of reach of children.If swallowed, get medical help or contact a Poison Control Center right away.

Directions

see important warnings under " When using this product"

- adults and children 2 years and over
- for cough suppression
- rub a thick layer on throat & chest &
- cover with a warm, dry cloth if desired
- keep clothing loose about throat and chest to help vapors reach the nose and mouth
- use up to three times daily or as directed by doctor
- for muscle / joint minor aches and pains apply to affected area not more than 3 to 4 times daily
- children under 2 years: do not use

Other information

- store at room temperature

Inactive ingredients

cedar wood oil, nutmeg oil, petrolatum, pine oil, thymol.

Manufactured for:

Akron Pharma Inc.

Fairfield, NJ 07004.

Call 1-877-225-6999

www.akronpharma.com